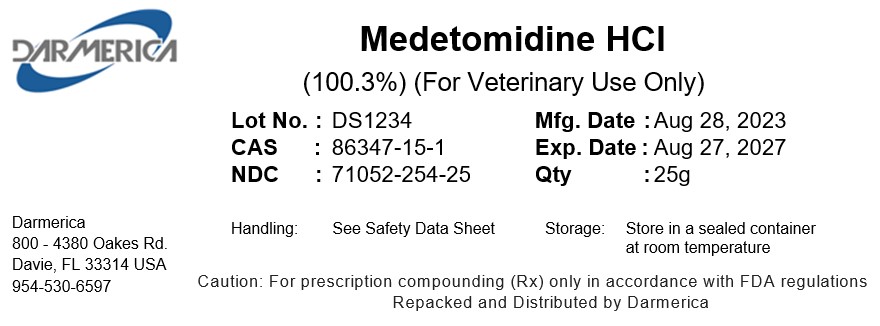 DRUG LABEL: Medetomidine HCl
NDC: 71052-254 | Form: POWDER
Manufacturer: DARMERICA, LLC
Category: other | Type: BULK INGREDIENT - ANIMAL DRUG
Date: 20241223

ACTIVE INGREDIENTS: MEDETOMIDINE HYDROCHLORIDE 1 kg/1 kg

Medetomidine HCl